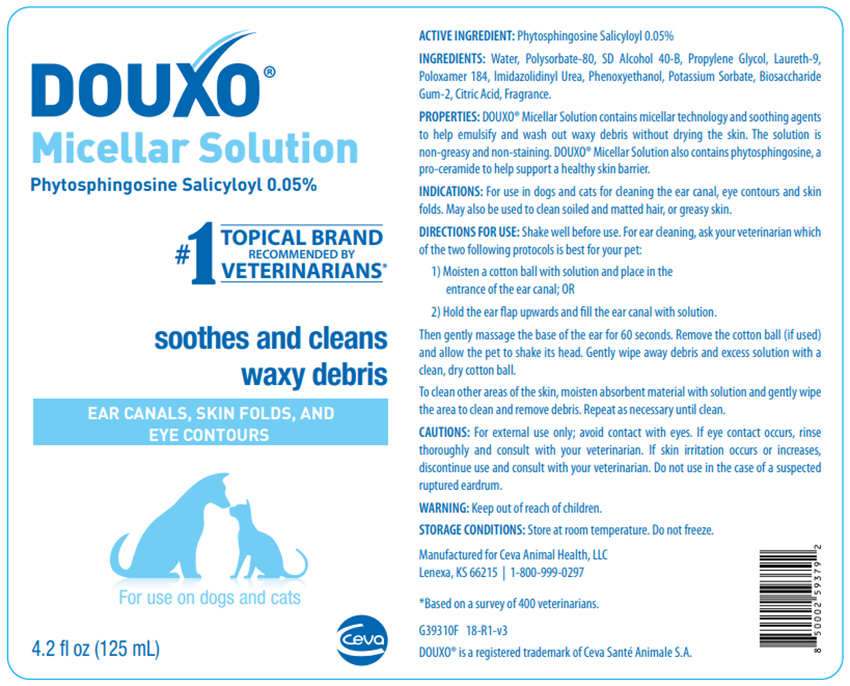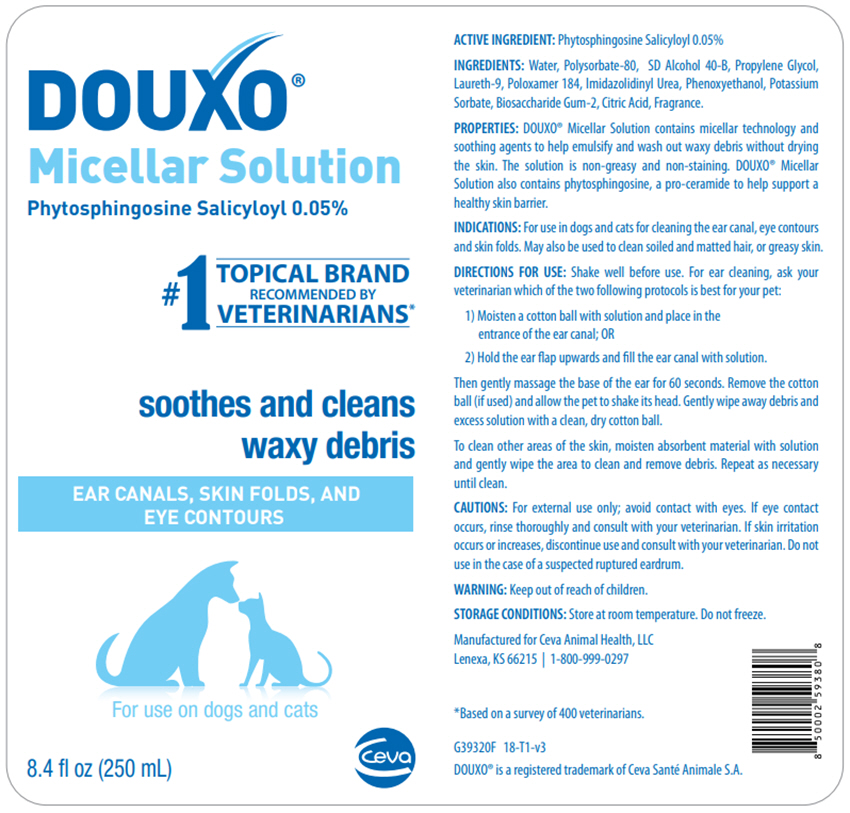 DRUG LABEL: DOUXO MICELLAR
NDC: 13744-158 | Form: SOLUTION
Manufacturer: Ceva Sante Animale
Category: animal | Type: OTC ANIMAL DRUG LABEL
Date: 20250905

ACTIVE INGREDIENTS: SALICYLOYL PHYTOSPHINGOSINE .5 mg/1 mL
INACTIVE INGREDIENTS: WATER; ALCOHOL; POLYSORBATE 80; PROPYLENE GLYCOL; LAURETH-9 PHOSPHATE; POLOXAMER 184; BIOSACCHARIDE GUM-2; IMIDUREA; PHENOXYETHANOL; POTASSIUM SORBATE; CITRIC ACID MONOHYDRATE

DOUXO® MICELLAR SOLUTION

ACTIVE INGREDIENT: Phytosphingosine Salicyloyl 0.05%

INGREDIENTS: Water, Polysorbate-80, SD Alcohol 40-B, Propylene Glycol, Laureth-9, Poloxamer 184, lmidazolidinyl Urea, Phenoxyethanol, Potassium Sorbate, Biosaccharide Gum-2, Citric Acid, Fragrance.

PROPERTIES: DOUXO® Micellar Solution contains micellar technology and soothing agents to help emulsify and wash out waxy debris without drying the skin. The solution is non-greasy and non-staining. DOUXO® Micellar Solution also contains phytosphingosine, a pro-ceramide to help support a healthy skin barrier.

VETERINARY INDICATIONS

INDICATIONS: For use in dogs and cats for cleaning the ear canal, eye contours and skin folds. May also be used to clean soiled and matted hair, or greasy skin.

DIRECTIONS FOR USE: Shake well before use. For ear cleaning, ask your veterinarian which of the two following protocols is best for your pet:

1) Moisten a cotton ball with solution and place in the entrance of the ear canal; OR
2) Hold the ear flap upwards and fill the ear canal with solution.

Then gently massage the base of the ear for 60 seconds. Remove the cotton ball (if used) and allow the pet to shake its head. Gently wipe away debris and excess solution with a clean, dry cotton ball.

To clean other areas of the skin, moisten absorbent material with solution and gently wipe the area to clean and remove debris. Repeat as necessary until clean.

WARNINGS

CAUTIONS: For external use only; avoid contact with eyes. If eye contact occurs, rinse thoroughly and consult with your veterinarian. If skin irritation occurs or increases, discontinue use and consult with your veterinarian. Do not use in the case of a suspected ruptured eardrum.

WARNING: Keep out of reach of children.

STORAGE AND HANDLING

STORAGE CONDITIONS: Store at room temperature. Do not freeze.

Manufactured for Ceva Animal Health, LLC
Lenexa, KS 66215 | 1-800-999-0297

*Based on a survey of 400 veterinarians.

G39320F 18-T1-v3

DOUXO® is a registered trademark of Ceva Santé Animale S.A.

PRINCIPAL DISPLAY PANEL - 125 mL Bottle Label

DOUXO®
Micellar Solution

Phytosphingosine Salicyloyl 0.05%

#1 TOPICAL BRAND
RECOMMENDED BY
VETERINARIANS*

soothes and cleans
waxy debris

EAR CANALS, SKIN FOLDS, AND
EYE CONTOURS

For use on dogs and cats

4.2 fl oz (125 mL)

CEVA

PRINCIPAL DISPLAY PANEL - 250 mL Bottle Label

DOUXO®
Micellar Solution

Phytosphingosine Salicyloyl 0.05%

#1 TOPICAL BRAND
RECOMMENDED BY
VETERINARIANS*

soothes and cleans
waxy debris

EAR CANALS, SKIN FOLDS, AND
EYE CONTOURS

For use on dogs and cats

8.4 fl oz (250 mL)

CEVA